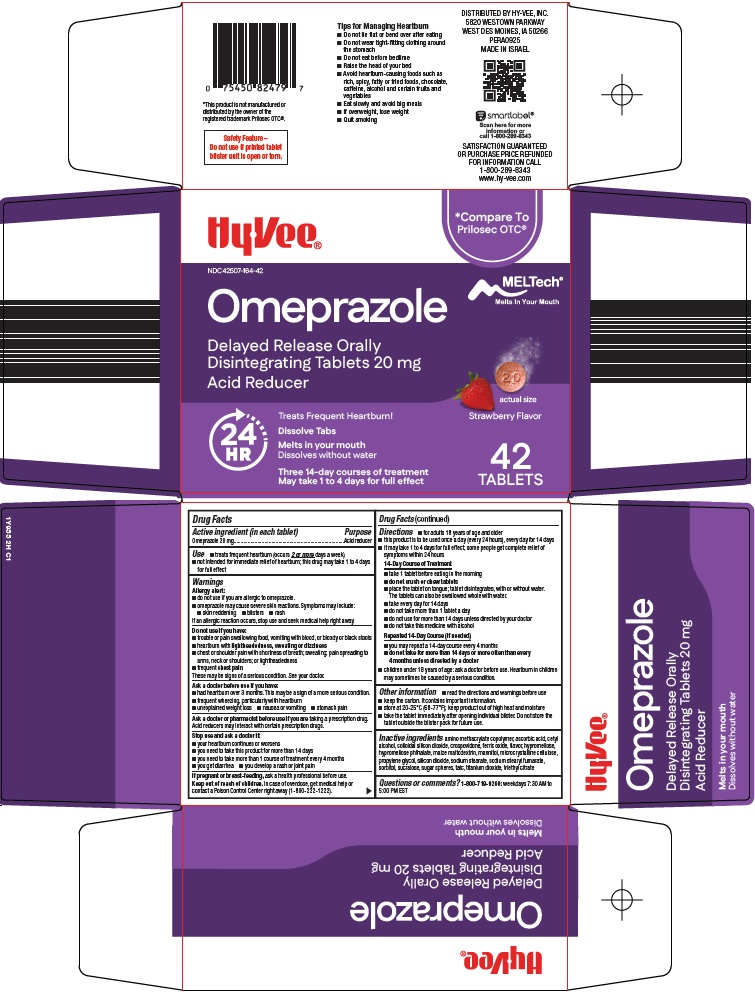 DRUG LABEL: omeprazole
NDC: 42507-164 | Form: TABLET, ORALLY DISINTEGRATING, DELAYED RELEASE
Manufacturer: HyVee Inc
Category: otc | Type: HUMAN OTC DRUG LABEL
Date: 20260201

ACTIVE INGREDIENTS: OMEPRAZOLE 20 mg/1 1
INACTIVE INGREDIENTS: DIMETHYLAMINOETHYL METHACRYLATE - BUTYL METHACRYLATE - METHYL METHACRYLATE COPOLYMER; ASCORBIC ACID; CETYL ALCOHOL; SILICON DIOXIDE; CROSPOVIDONE, UNSPECIFIED; FERRIC OXIDE RED; HYPROMELLOSE, UNSPECIFIED; MALTODEXTRIN; MANNITOL; MICROCRYSTALLINE CELLULOSE; PROPYLENE GLYCOL; SODIUM STEARATE; SODIUM STEARYL FUMARATE; SORBITOL; SUCRALOSE; TALC; TITANIUM DIOXIDE; TRIETHYL CITRATE

Hy-Vee, Inc. Omeprazole Drug Facts

Active ingredient (in each tablet)

Omeprazole 20 mg

Purpose

Acid reducer

Use

- treats frequent heartburn (occurs 2 or more days a week)
- not intended for immediate relief of heartburn; this drug may take 1 to 4 days for full effect

Warnings

Allergy alert:

- do not use if you are allergic to omeprazole.
- omeprazole may cause severe skin reactions. Symptoms may include:
- skin reddening
- blisters
- rash

If an allergic reaction occurs, stop use and seek medical help right away.

Do not use if you have:

- trouble or pain swallowing food, vomiting with blood, or bloody or black stools
- heartburn with lightheadedness, sweating or dizziness
- chest or shoulder pain with shortness of breath; sweating; pain spreading to arms, neck or shoulders; or lightheadedness
- frequent chest pain

These may be signs of a serious condition. See your doctor.

Ask a doctor before use if you have:

- had heartburn over 3 months. This may be a sign of a more serious condition.
- frequent wheezing, particularly with heartburn
- unexplained weight loss
- nausea or vomiting
- stomach pain

Ask a doctor or pharmacist before use if you are

taking a prescription drug. Acid reducers may interact with certain prescription drugs.

Stop use and ask a doctor if:

- your heartburn continues or worsens
- you need to take this product for more than 14 days
- you need to take more than 1 course of treatment every 4 months
- you get diarrhea
- you develop a rash or joint pain

If pregnant or breast-feeding,

ask a health professional before use.

Keep out of reach of children.

In case of overdose, get medical help or contact a Poison Control Center right away (1-800-222-1222).

Directions

- for adults 18 years of age and older
- this product is to be used once a day (every 24 hours), every day for 14 days
- it may take 1 to 4 days for full effect; some people get complete relief of symptoms within 24 hours

14-Day Course of Treatment

- take 1 tablet before eating in the morning
- do not crush or chew tablets
- place the tablet on tongue; tablet disintegrates, with or without water. The tablets can also be swallowed whole with water.
- take every day for 14 days
- do not take more than 1 tablet a day
- do not use for more than 14 days unless directed by your doctor
- do not take this medicine with alcohol

Repeated 14-Day Course (if needed)

- you may repeat a 14-day course every 4 months
- do not take for more than 14 days or more often than every 4 months unless directed by a doctor
- children under 18 years of age: ask a doctor before use. Heartburn in children may sometimes be caused by a serious condition.

Other information

- read the directions and warnings before use
- keep the carton. It contains important information.
- store at 20-25°C (68-77°F); keep product out of high heat and moisture
- take tablet immediately after opening individual blister. Do not store the tablet outside the blister pack for future use.

Inactive ingredients

amino methacrylate copolymer, ascorbic acid, cetyl alcohol, colloidal silicon dioxide, crospovidone, ferric oxide, flavor, hypromellose, hypromellose phthalate, maize maltodextrin, mannitol, microcrystalline cellulose, propylene glycol, silicon dioxide, sodium stearate, sodium stearyl fumarate, sorbitol, sucralose, sugar spheres, talc, titanium dioxide, triethyl citrate

Questions or comments?

1-800-719-9260: weekdays 7:30 AM to 5:00 PM EST

Package/Label Principal Display Panel

Hy•Vee®

Compare To Prilosec OTC®

MELTech®

Melts In Your Mouth

Omeprazole

Delayed Release Orally Disintegrating Tablets 20 mg

Acid Reducer

actual size

Strawberry Flavor

24 HR

Treats Frequent Heartburn!

Dissolve Tabs

Melts in your mouth

Dissolves without water

Three 14-day courses of treatment

May take 1 to 4 days for full effect

42 TABLETS